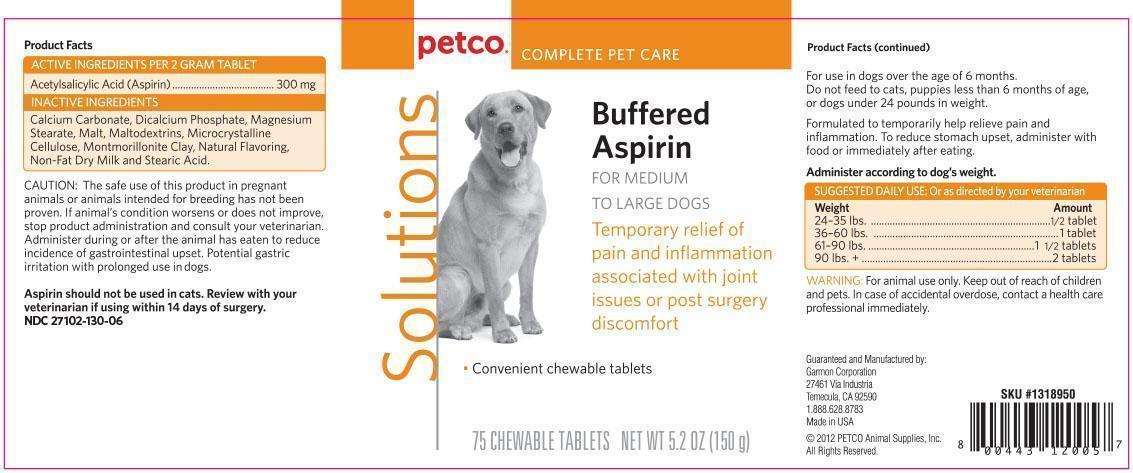 DRUG LABEL: Buffered Aspirin
NDC: 27102-130 | Form: TABLET, CHEWABLE
Manufacturer: Petco
Category: animal | Type: OTC ANIMAL DRUG LABEL
Date: 20130711

ACTIVE INGREDIENTS: Aspirin 300 mg/1 1
INACTIVE INGREDIENTS: CALCIUM CARBONATE; BARLEY MALT SYRUP; CELLULOSE, MICROCRYSTALLINE; STEARIC ACID; MAGNESIUM STEARATE; SKIM MILK; MONTMORILLONITE; ANHYDROUS DIBASIC CALCIUM PHOSPHATE; MALTODEXTRIN

Buffered Aspirin For Medium to Large Dogs

ACTIVE INGREDIENT

Product Facts

Active Ingredients per 2 gram tablet:
Acetylsalicylic Acid (Aspirin)................................300 mg

Inactive Ingredients: Calcium Carbonate, Dicalcium
Phosphate, Magnesium Stearate, Malt, Maltodextrins,
Microcrystalline Cellulose, Montmorillonite Clay,
Natural Flavoring, Non-Fat Dry Milk, and Stearic Acid.

PRECAUTIONS

Caution: The safe use of this product in pregnant animals or animals
intended for breeding has not been proven. If
animal’s condition worsens or does not improve, stop
product administration and consult your veterinarian.
Administer during or after the animal has eaten to
reduce incidence of gastrointestinal upset. Potential gastric irritation with prolonged use in dogs.

Aspirin should not be used in cats. Review with your
veterinarian if using within 14 days of surgery.

DOSAGE AND ADMINISTRATION

Product Facts (continued)

For use in dogs over the age of 6 months.
Do not feed to cats, puppies less than 6 months of age,
or dogs under 24 pounds in weight.

Formulated to help temporary
relieve pain and inflammation. To reduce stomach
upset, give with food or immediately after.

Administer according to dog's weight.
Suggested Daily Use: Or as directed by your veterinarian
Weight Amount
24-35 lbs 1/2 tablet
36-60 lbs 1 tablet
61-90 lbs 1 1/2 tablets
90+ lbs 2 tablets

WARNINGS

Warning: For animal use only. Keep out of reach of
children and other animals. In case of accidental
overdose, contact a health professional immediately.